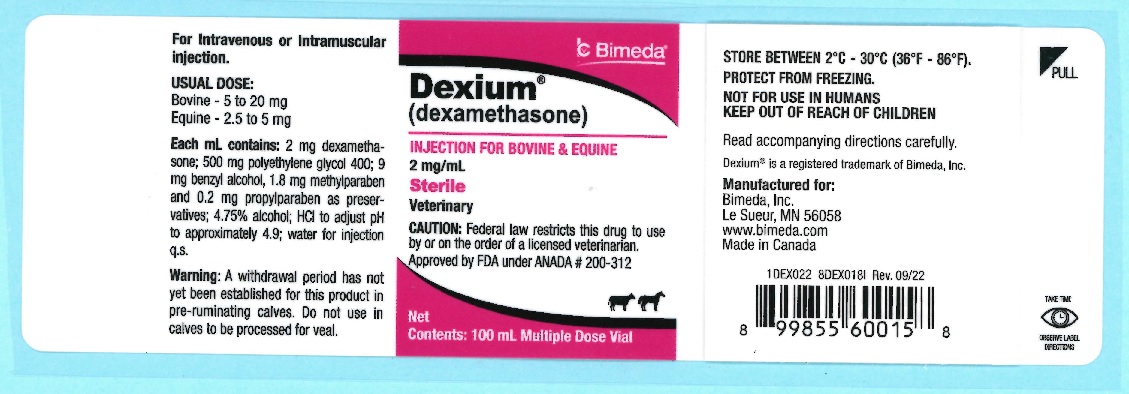 DRUG LABEL: Dexium
NDC: 61133-0899 | Form: INJECTION, SOLUTION
Manufacturer: Bimeda, Inc.
Category: animal | Type: PRESCRIPTION ANIMAL DRUG LABEL
Date: 20240423

ACTIVE INGREDIENTS: Dexamethasone 2 mg/1 mL
INACTIVE INGREDIENTS: Propylparaben

DESCRIPTION

Dexium®
(dexamethasone)
2 mg/mL
For intravenous or intramuscular injection
Veterinary
NOT FOR USE IN HUMANS
KEEP OUT OF REACH OF CHILDREN

CAUTION: Federal law restricts this drug to use by or on the order of a licensed veterinarian.

DESCRIPTION: Dexium (dexamethasone) is a synthetic analogue of prednisolone, having similar but more potent anti-inflammatory therapeutic action and diversified hormonal and metabolic effects. Modification of the basic corticoid structure as achieved in Dexium offers enhanced anti-inflammatory effect compared to older corticosteroids. The dosage of Dexium required is markedly lower than that of prednisone and prednisolone.

Dexium is not species-specific; however, the veterinarian should read the sections on INDICATIONS, DOSAGE, SIDE EFFECTS, CONTRAINDICATIONS, PRECAUTIONS, and WARNINGS before this drug is used.

Dexium is intended for intravenous or intramuscular administration. Each mL contains 2 mg dexamethasone, 500 mg polyethylene glycol 400, 9 mg benzyl alcohol, 1.8 mg methylparaben and 0.2 mg propylparaben as preservatives, 4.75% alcohol, HCl to adjust pH to approximately 4.9, water for injection q.s.

CLINICAL STUDIES

EXPERIMENTAL STUDIES: Experimental animal studies on dexamethasone have revealed it possesses greater anti-inflammatory activity than many steroids. Veterinary clinical evidence indicates dexamethasone has approximately 20 times the anti-inflammatory activity of prednisolone and 70 to 80 times that of hydrocortisone. Thymus involution studies show dexamethasone possesses 25 times the activity of prednisolone. In reference to mineralcorticoid activity, dexamethasone does not cause significant sodium or water retention. Metabolic balance studies show that animals on controlled and limited protein intake will exhibit nitrogen losses on exceedingly high dosages.

INDICATIONS AND USAGE

INDICATIONS: Dexium is indicated for the treatment of primary bovine ketosis and as an anti-inflammatory agent in the bovine and equine.
As supportive therapy, Dexium may be used in the management of various rheumatic, allergic, dermatologic, and other diseases known to be responsive to anti-inflammatory corticosteroids. Dexium may be used intravenously as supportive therapy when an immediate hormonal response is required.

Bovine Ketosis
Dexium is offered for the treatment of primary ketosis. The gluconeogenic effects of Dexium, when administered intramuscularly, are generally noted within the first 6 to 12 hours. When Dexium is used intravenously, the effects may be noted sooner. Blood sugar levels rise to normal levels rapidly and generally rise to above normal levels within 12 to 24 hours. Acetone bodies are reduced to normal concentrations usually within 24 hours. The physical attitude of animals treated with Dexium brightens and appetite improves, usually within 12 hours. Milk production, which is suppressed as a compensatory reaction in this condition, begins to increase. In some instances, it may even surpass previous peaks. The recovery process usually takes from 3 to 7 days.

Supportive Therapy
Dexium may be used as supportive therapy in mastitis, metritis, traumatic gastritis, and pyelonephritis, while appropriate primary therapy is administered. In these cases, the corticosteroid combats accompanying stress and enhances the feeling of general well-being.
Dexium may also be used as supportive therapy in inflammatory conditions such as arthritic conditions, snake bite, acute mastitis, shipping fever, pneumonia, laminitis, and retained placenta.

Equine
Dexium is indicated for the treatment of acute musculoskeletal inflammations, such as bursitis, carpitis, osselets, tendonitis, myositis, and sprains. If boney changes exist in any of these conditions, joints or accessory structures, a response to Dexium cannot be expected. In addition, Dexium may be used as supportive therapy in fatigue, heat exhaustion, influenza, laminitis, and retained placenta provided that the primary cause is determined and corrected.

DOSAGE AND ADMINISTRATION

ADMINISTRATION AND DOSAGE: Therapy with Dexium, as with any other potent corticosteroid, should be individualized according to the severity of the condition being treated, anticipated duration of steroid therapy, and animal's threshold or tolerance for steroid excess.
Treatment may be changed over to Dexium from any other glucocorticoid with proper reduction or adjustment of dosage.

Bovine: Dexium: 5 - 20 mg intravenously or intramuscularly.

Equine: Dexium: 2.5 - 5 mg intravenously or intramuscularly.

CONTRAINDICATIONS

CONTRAINDICATIONS: Except for emergency therapy, do not use in animals with chronic nephritis and hyper-corticalism (Cushing's syndrome). Existence of congestive heart failure, diabetes, and osteoporosis are relative contraindications. Do not use in viral infections during with viremic stage.

PRECAUTIONS

PRECAUTIONS: Animals receiving Dexium should be under close observation. Because of the anti-inflammatory action of corticosteroids, signs of infection may be masked and it may be necessary to stop treatment until a further diagnosis is made. Overdosage of some glucocorticoids may result in sodium retention, fluid retention, potassium loss, and weight gain.

Dexium may be administered to animals with acute or chronic bacterial infections providing the infections are controlled with appropriate antibiotic or chemotherapeutic agents.

Doses greater than those recommended in horses may produce transient drowsiness or lethargy in some horses. The lethargy usually abates in 24 hours. Use of corticosteroids, depending on the dose, duration, and specified steroid, may result in inhibition of endogenous steroid production following drug withdrawal. In patients presently receiving or recently withdrawn from systemic corticosteroid treatments, therapy with a rapidly acting corticosteroid should be considered in unusually stressful situations.

WARNINGS

WARNINGS: Clinical and experimental data have demonstrated that corticosteroids administered orally or parenterally to animals may induce the first stage of parturition when administered during the last trimester of pregnancy and may precipitate premature parturition followed by dystocia, fetal death, retained placenta, and metritis.
Additionally, corticosteroids administered to dogs, rabbits, and rodents during pregnancy have produced cleft palate. Other congenital anomalies including deformed forelegs, phocomelia, and anasarca have been reported in offspring of dogs which received corticosteroids during pregnancy.

A withdrawal period has not been established for this product in pre-ruminating calves. Do not use in calves to be processed for veal.

SIDE EFFECTS: Side effects, such as SAP and SGPT enzyme elevations, weight loss, anorexia, polydipsia, and polyuria, have occurred following the use of corticosteroids in dogs. Vomiting and diarrhea (occasionally bloody) have been observed in cats and dogs. Cushing's syndrome in dogs has been reported in association with prolonged or repeated steroid therapy. Corticosteroids reportedly cause laminitis in horses.

To report suspected adverse drug events, for technical assistance or to obtain a copy of the Safety Data Sheet (SDS), contact Bimeda, Inc. at 1-888-524-6332. For additional information about adverse drug experience reporting for animal drugs, contact FDA at 1-888-FDA-VETS or online at www.fda.gov/reportanimalae.

HOW SUPPLIED

HOW SUPPLIED: Dexium, 2 mg per mL, 100 mL multiple dose vial.

STORAGE AND HANDLING

STORE BETWEEN 2°C-30°C (36°F-86°F). PROTECT FROM FREEZING.

Approved by FDA under ANADA # 200-312